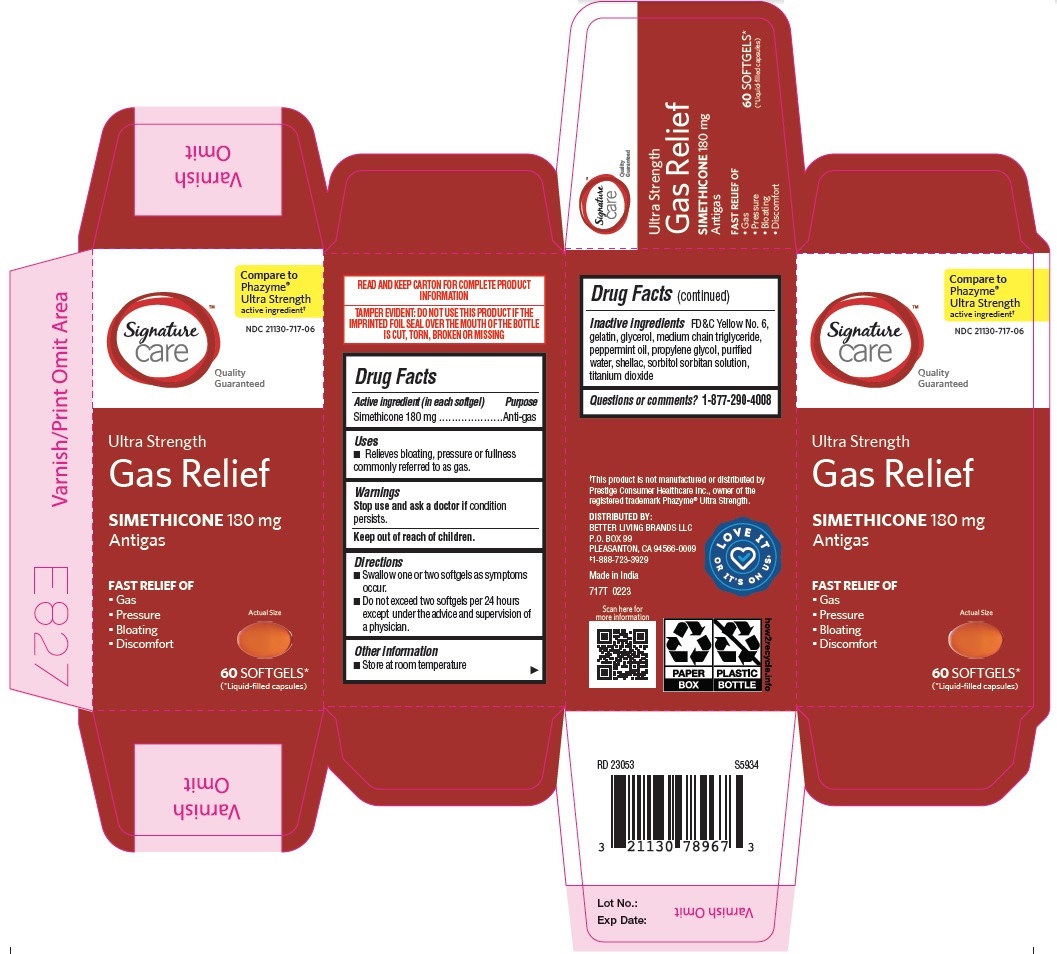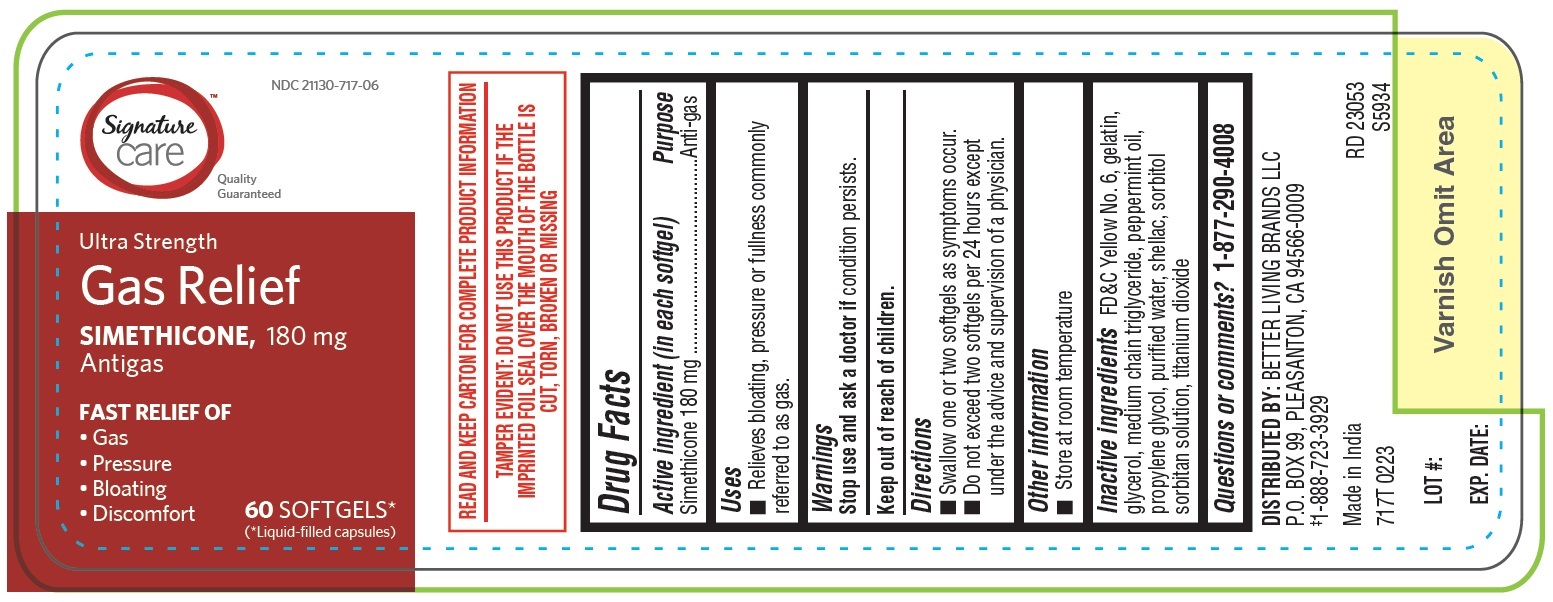 DRUG LABEL: Ultra Strength Gas Relief
NDC: 21130-717 | Form: CAPSULE
Manufacturer: BETTER LIVING BRANDS, LLC
Category: otc | Type: HUMAN OTC DRUG LABEL
Date: 20250212

ACTIVE INGREDIENTS: DIMETHICONE 180 mg/1 1
INACTIVE INGREDIENTS: SORBITAN; SORBITOL SOLUTION; GELATIN; TITANIUM DIOXIDE; PROPYLENE GLYCOL; WATER; PEPPERMINT OIL; FD&C YELLOW NO. 6; SHELLAC; MEDIUM-CHAIN TRIGLYCERIDES; GLYCERIN

717T Albertsons 21130-717 Simethicone soft gelatin capsules 180 mg

Active ingredient (in each softgel)
Simethicone 180 mg

Purpose
Anti-gas

Uses

- Relieves bloating, pressure or fullness commonly referred to as gas.

Warnings

Stop use and ask a doctor if condition persists.

Keep out of reach of children.

Directions
• Swallow one or two softgels as symptoms occur.
• Do not exceed two softgels per 24 hours except under the advice and supervision of a physician.

Other information
• Store at room temperature

Inactive ingredients
FD&C Yellow No. 6, gelatin, glycerol, medium chain triglyceride, peppermint oil, propylene glycol, purified water, shellac, sorbitol sorbitan solution, titanium dioxide

Questions or comments?1-877-290-4008